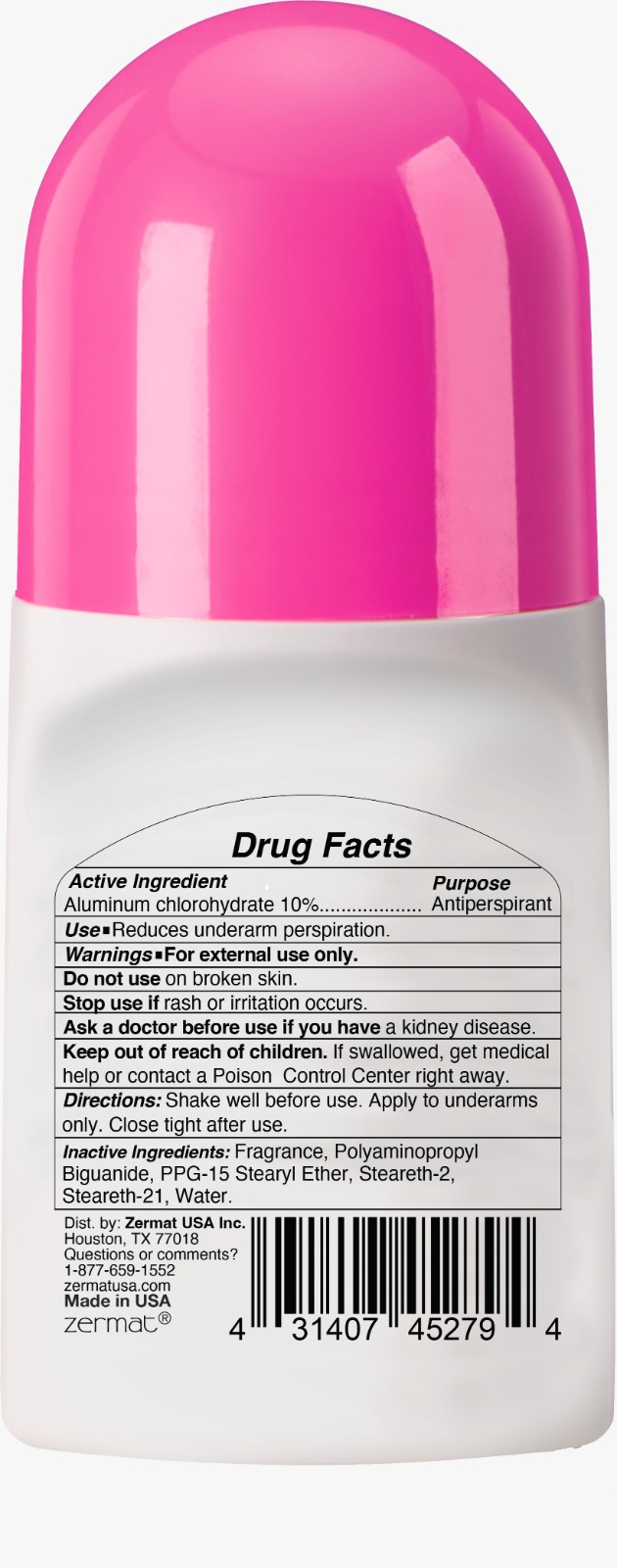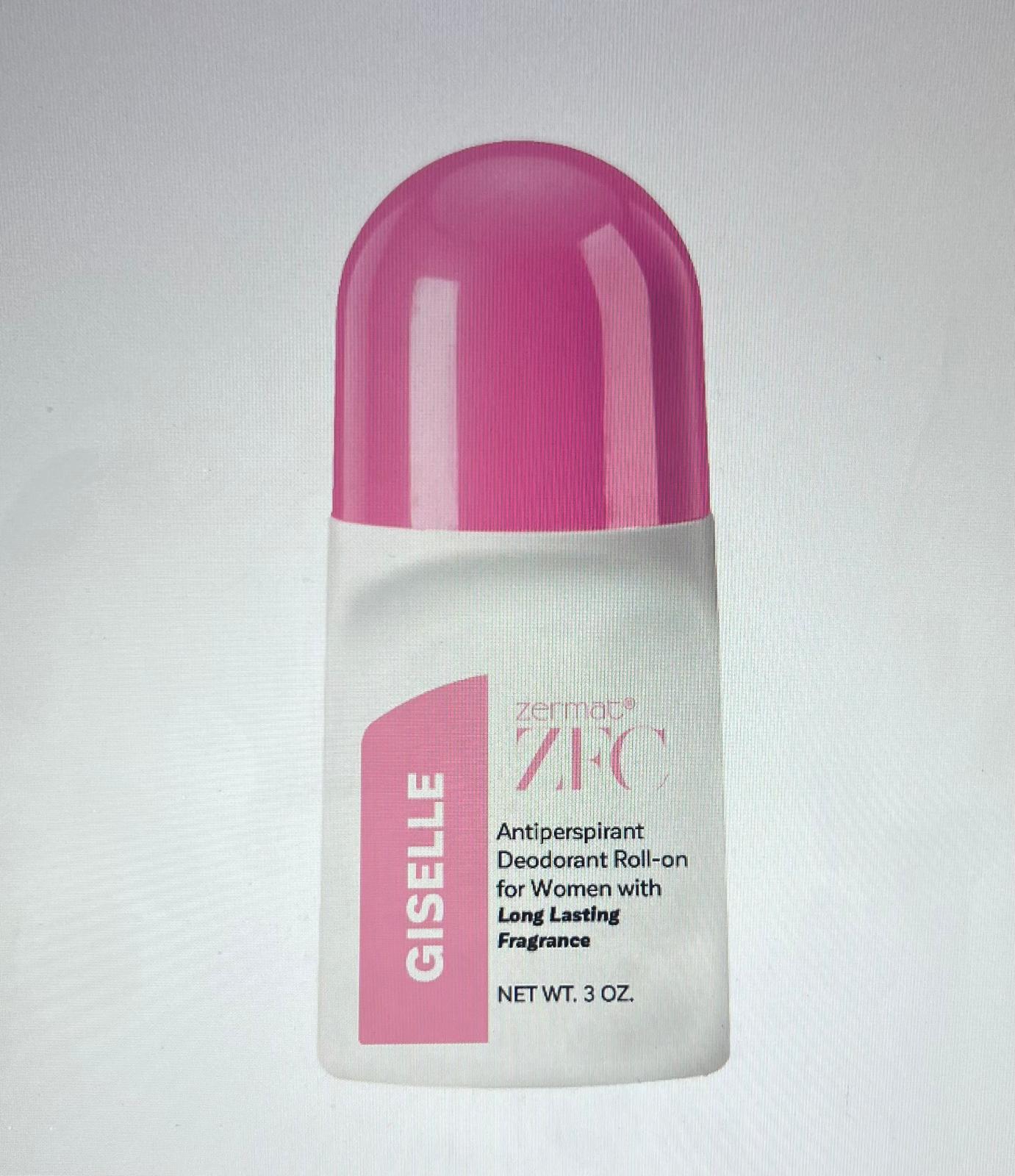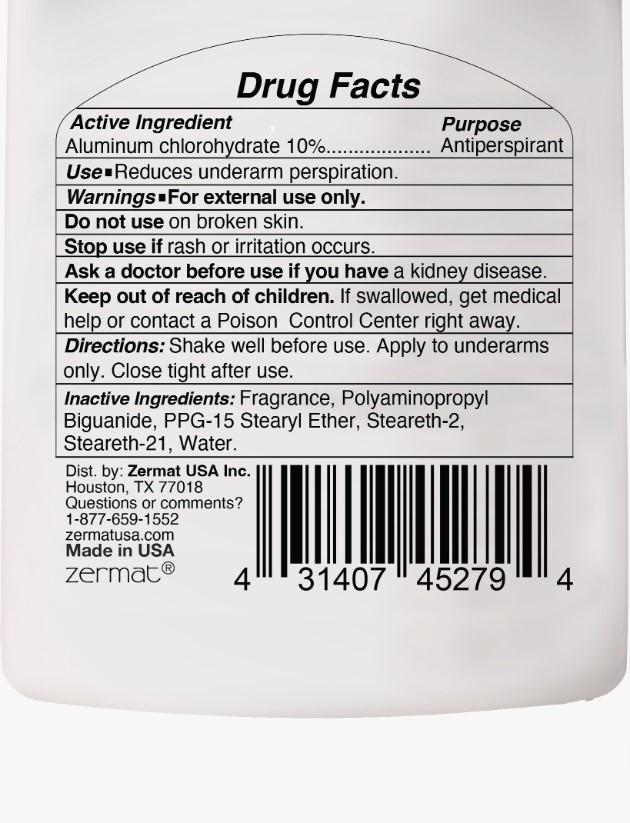 DRUG LABEL: GISELLE ANTIPERSPIRANT DEODORANT ROLL-ON FOR WOMEN
NDC: 84178-011 | Form: CREAM
Manufacturer: EVI LABS
Category: otc | Type: HUMAN OTC DRUG LABEL
Date: 20260116

ACTIVE INGREDIENTS: ALUMINUM CHLOROHYDRATE 8.5 g/85 g
INACTIVE INGREDIENTS: STEARETH-2 3.4 g/85 g; FRAGRANCE FLORAL ORC0902236 1.7 g/85 g; PPG-15 STEARYL ETHER 3.4 g/85 g; WATER 65.918 g/85 g; STEARETH-21 1.913 g/85 g; POLYAMINOPROPYL BIGUANIDE 0.17 g/85 g

GISELLE ANTIPERSPIRANT DEODORANT ROLL-ON FOR WOMEN

ACTIVE INGREDIENT

ALUMINUM CHLOROHYDRATE 10%

PURPOSE

ANTIPERSPIRANT

USE

REDUCES UNDERARM PERSPIRATION

WARNING

FOR EXTERNAL USE ONLY

DIRECTIONS

Shake well before use. Apply to underarms only. Close tight after use.

INACTIVE INGREDIENTS

Fragrance, Poly aminopropyl Biguanide, PPG-15 Stearyl Ether, Steareth-2, Steareth-21, Water

Do not use on broken skin.

Stop use if rash or irritation occurs.

DOSAGE AND ADMINISTRATION

Apply to underarms only

KEEP OUT OF REACH OF CHILDREN

IF SWALLOWED, GET MEDICAL HELP OR CONTACT A POISON CONTROL CENTER RIGHT AWAY.